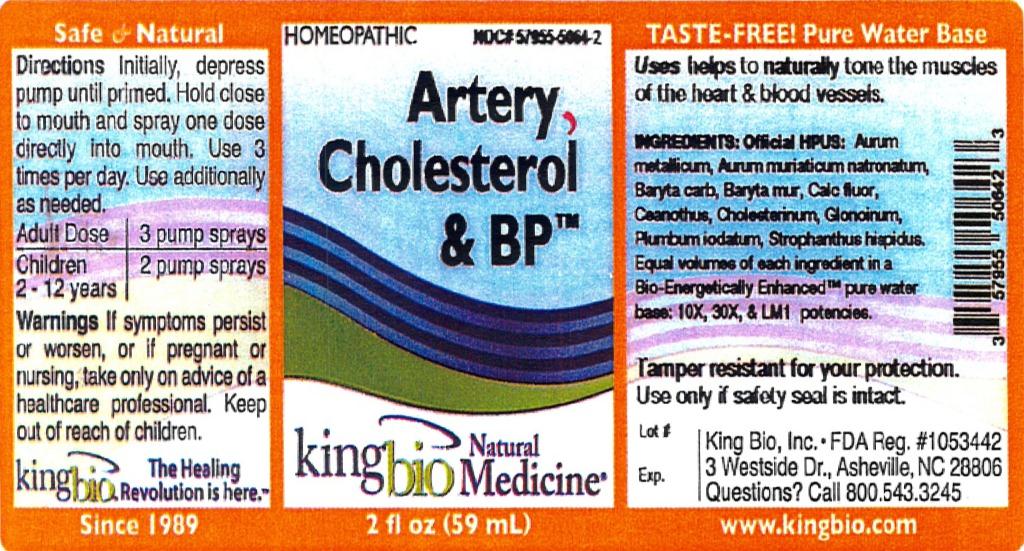 DRUG LABEL: Artery Cholesterol and BP
NDC: 57955-5064 | Form: LIQUID
Manufacturer: King Bio Inc.
Category: homeopathic | Type: HUMAN OTC DRUG LABEL
Date: 20120319

ACTIVE INGREDIENTS: GOLD 10 [hp_X]/59 mL; SODIUM TETRACHLOROAURATE 10 [hp_X]/59 mL; BARIUM CARBONATE 10 [hp_X]/59 mL; BARIUM CHLORIDE DIHYDRATE 10 [hp_X]/59 mL; CALCIUM FLUORIDE 10 [hp_X]/59 mL; CEANOTHUS AMERICANUS LEAF 10 [hp_X]/59 mL; CHOLESTEROL 10 [hp_X]/59 mL; NITROGLYCERIN 10 [hp_X]/59 mL; LEAD IODIDE 10 [hp_X]/59 mL; STROPHANTHUS HISPIDUS SEED 10 [hp_X]/59 mL
INACTIVE INGREDIENTS: WATER

Artery Cholesterol and BP

Active Ingredients

Official HPUS: Aurum metallicum, Aurum muriaticum natronatum, Baryta carbonica, Baryta muriatica, Calcarea flourica, Ceanothus americanus, Cholesterinum, Glonoinum, Plumbum iodatum, Strophanthus.

Reference image: arterycholesterolandbp.jpg

Inactive Ingredient

Equal volumes of each ingredient in a Bio-Energetically Enhanced pure water base: 10X, 30X, and LM1 potencies.
Reference image: arterycholesterolandbp.jpg

Purposes

Uses helps to naturally tone the muscles of the heart and blood vessels.

Reference image: arterycholesterolandbp.jpg

Directions

Initially, depress pump until primed. Hold close to mouth and spray one dose directly into mouth. Use 3 times per day. Use additionally as needed.

Adult dose - 3 pump sprays

Children 2-12 years - 2 pump sprays

Reference image: arterycholesterolandbp.jpg

Warnings

If symptoms persist or worsen, or if pregnant or nursing, take only on advice of a healthcare professional.

Tamper resistant for your protection. Use only if safety seal is intact.

Reference image: arterycholesterolandbp.jpg

Keep out of reach of children.

Reference image: arterycholesterolandbp.jpg

Uses

Uses helps to naturally tone the muscles of the heart and blood vessels.

Reference image: arterycholesterolandbp.jpg

Package Label

King Bio, Inc.

3 Westside Dr

Asheville, NC 28806

Questions? Call 800.543.3245

www.kingbio.com